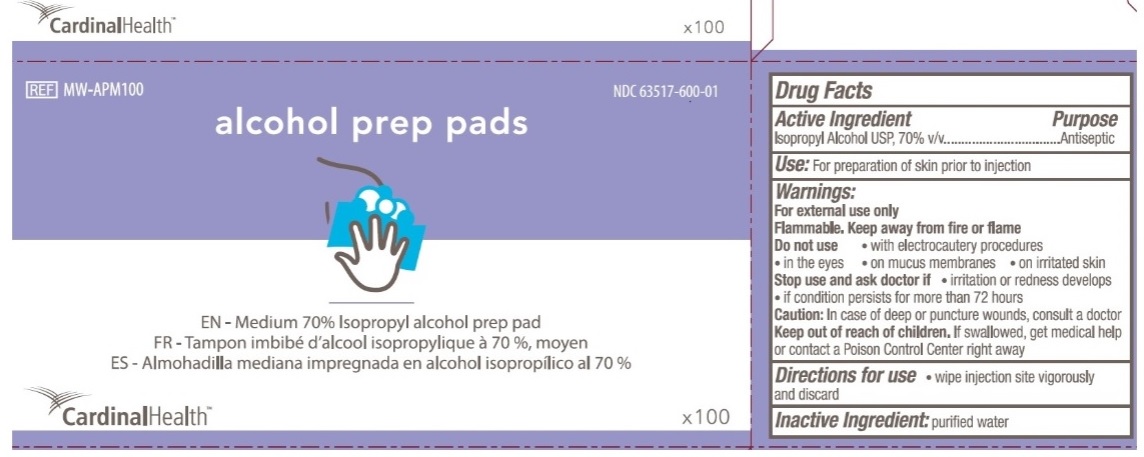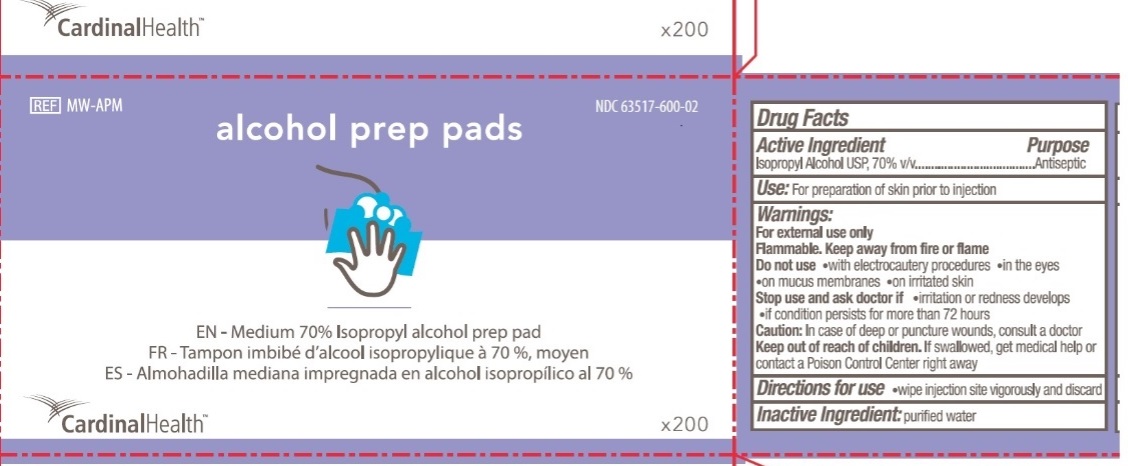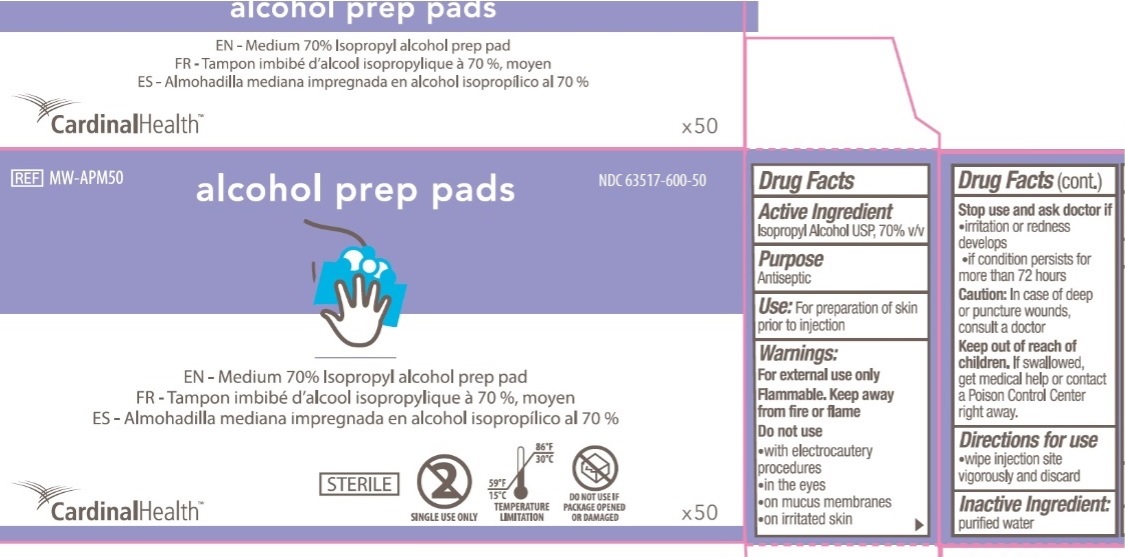 DRUG LABEL: Alcohol Prep Pads
NDC: 63517-600 | Form: SWAB
Manufacturer: Cardinal Health 200, Inc.
Category: otc | Type: HUMAN OTC DRUG LABEL
Date: 20251023

ACTIVE INGREDIENTS: ISOPROPYL ALCOHOL 70 mL/100 mL
INACTIVE INGREDIENTS: WATER

Cardinal Medium Alcohol Prep Pads

Active Ingredients

Isopropyl Alcohol USP, 70% v/v

Purpose

Antiseptic

Uses

For preparation of skin prior to injection

Warnings

For external use only

Flammable. Keep away from fire or flame

Do not use

- with electrocautery procedures
- in the eyes
- on mucus membrane
- on irritated skin

Stop use and ask doctor if

- irritation or redness develops
- if condition persists for more than 72 hours

Caution

In case of deep or punctured wounds, consult a doctor

Keep out of reach of children

If swallowed, get medical help or contact a Poison Control Center right away

Directions for use

- wipe injection site vigorously and discard

Inactive Ingredient

purified water

Principal Display Panel

CardinalHealth

NDC 63517-600-01

REF MW-APM100

alcohol prep pads

EN - Medium 70% Isopropyl alcohol prep pad

FR - Tampon imbibe d'alcool isopropylique a 70%, moyen

ES - Almohadilla mediana impregnada en alcohol isopropilico al 70%

CardinalHealth

X100

CardinalHealth

NDC 63517-600-02

REF MW-APM

alcohol prep pads

EN - Medium 70% Isopropyl alcohol prep pad

FR - Tampon imbibe d'alcool isopropylique a 70%, moyen

ES - Almohadilla mediana impregnada en alcohol isopropilico al 70%

CardinalHealth

X200

CardinalHealth

NDC 63517-600-50

REF MW-APM50

alcohol prep pads

EN - Medium 70% Isopropyl alcohol prep pad

FR - Tampon imbibe d'alcool isopropylique a 70%, moyen

ES - Almohadilla mediana impregnada en alcohol isopropilico al 70%

CardinalHealth

X50